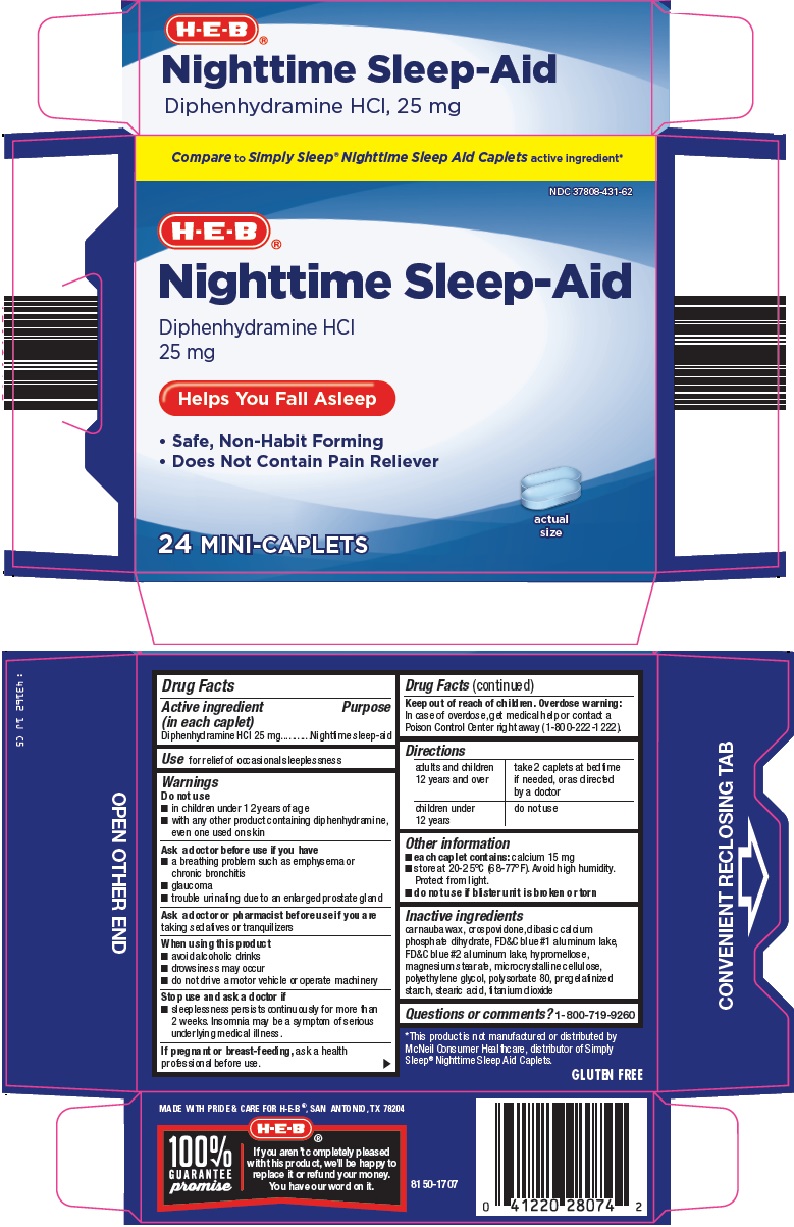 DRUG LABEL: nighttime sleep aid
NDC: 37808-431 | Form: TABLET, FILM COATED
Manufacturer: H E B
Category: otc | Type: HUMAN OTC DRUG LABEL
Date: 20251125

ACTIVE INGREDIENTS: DIPHENHYDRAMINE HYDROCHLORIDE 25 mg/1 1
INACTIVE INGREDIENTS: CARNAUBA WAX; CROSPOVIDONE (120 .MU.M); DIBASIC CALCIUM PHOSPHATE DIHYDRATE; FD&C BLUE NO. 1; FD&C BLUE NO. 2; HYPROMELLOSE, UNSPECIFIED; MAGNESIUM STEARATE; MICROCRYSTALLINE CELLULOSE; POLYETHYLENE GLYCOL, UNSPECIFIED; POLYSORBATE 80; STEARIC ACID; TITANIUM DIOXIDE

HEB Nighttime Sleep Aid Drug Facts

Active ingredient (in each caplet)

Diphenhydramine HCl 25 mg

Purpose

Nighttime sleep-aid

Use

for relief of occasional sleeplessness

Warnings

Do not use

1. in children under 12 years of age
2. with any other product containing diphenhydramine, even one used on skin

Ask a doctor before use if you have

1. a breathing problem such as emphysema or chronic bronchitis
2. glaucoma
3. trouble urinating due to an enlarged prostate gland

Ask a doctor or pharmacist before use if you are

taking sedatives or tranquilizers

When using this product

- avoid alcoholic drinks
- drowsiness may occur
- do not drive a motor vehicle or operate machinery

Stop use and ask a doctor if

- sleeplessness persists continuously for more than 2 weeks. Insomnia may be a symptom of serious underlying medical illness.

If pregnant or breast-feeding,

ask a health professional before use.

Keep out of reach of children. Overdose warning:

In case of overdose, get medical help or contact a Poison Control Center right away (1-800-222-1222).

Directions

adults and children 12; years and over | take 2 caplets at bedtime if needed, or as directed by a doctor
children under 12 years | do not use

Other information

- each caplet contains: calcium 15 mg
- store at 20-25°C (68-77°F). Avoid high humidity. Protect from light.
- do not use if blister unit is broken or torn

Inactive ingredients

carnauba wax, crospovidone, dibasic calcium phosphate dihydrate, FD&C blue #1 aluminum lake, FD&C blue #2 aluminum lake, hypromellose, magnesium stearate, microcrystalline cellulose, polyethylene glycol, polysorbate 80, pregelatinized starch, stearic acid, titanium dioxide

Questions or comments?

1-800-719-9260

Principal Display Panel

Compare to Simply Sleep® Nighttime Sleep Aid Caplets active ingredient

Nighttime Sleep-Aid

Diphenhydramine HCl 25 mg

Helps You Fall Asleep

Safe, Non-Habit Forming

Does Not Contain Pain Reliever

actual size

24 MINI-CAPLETS